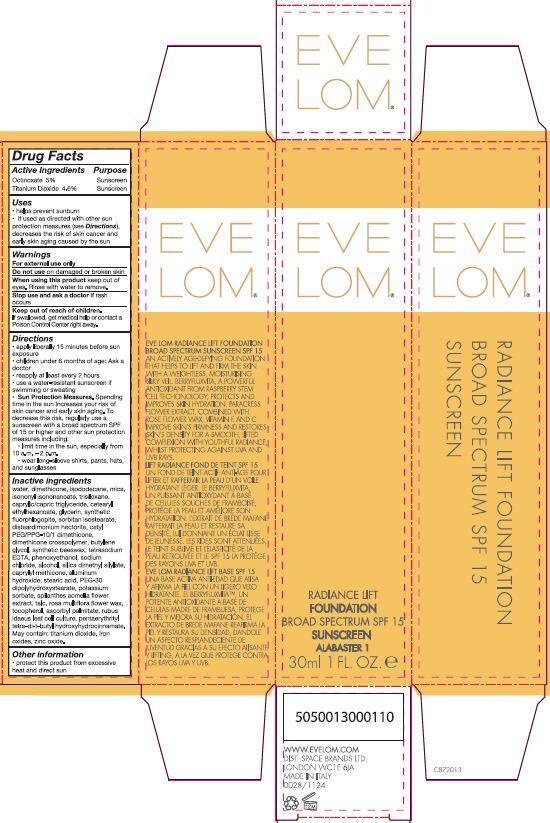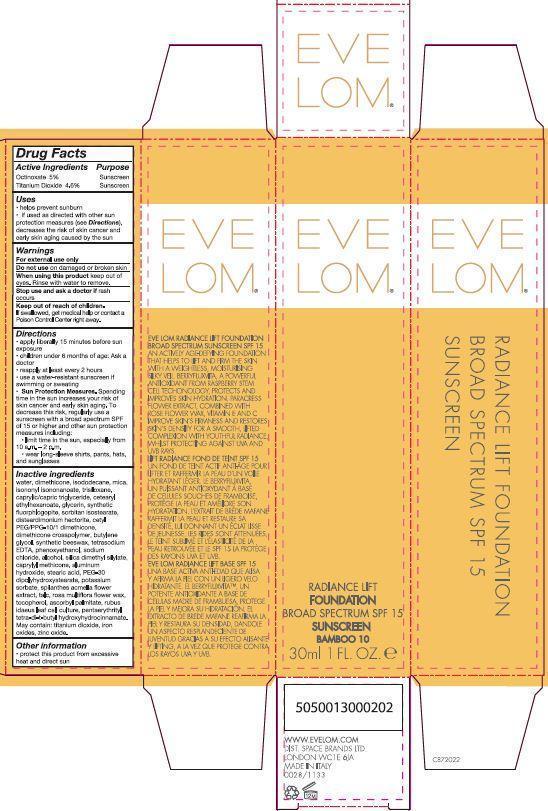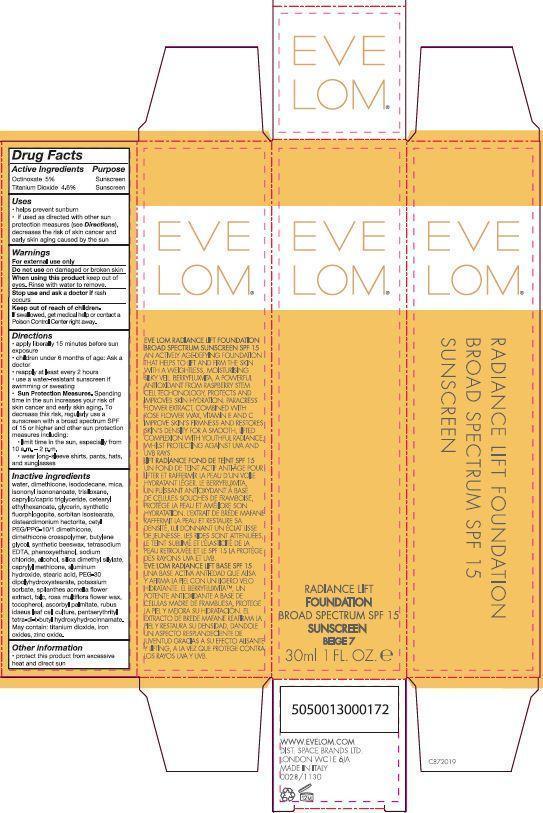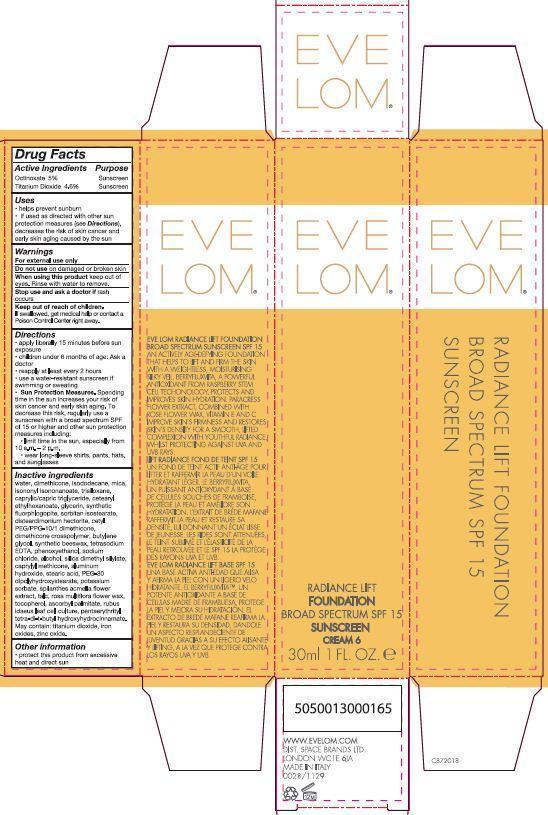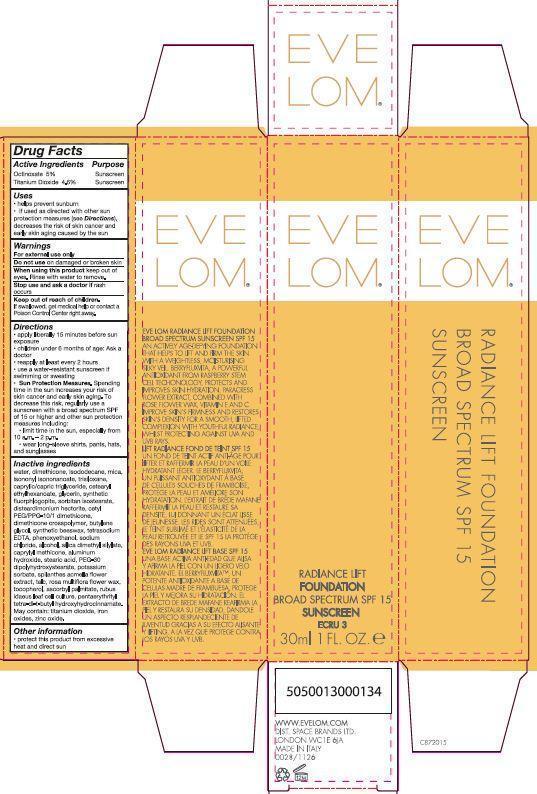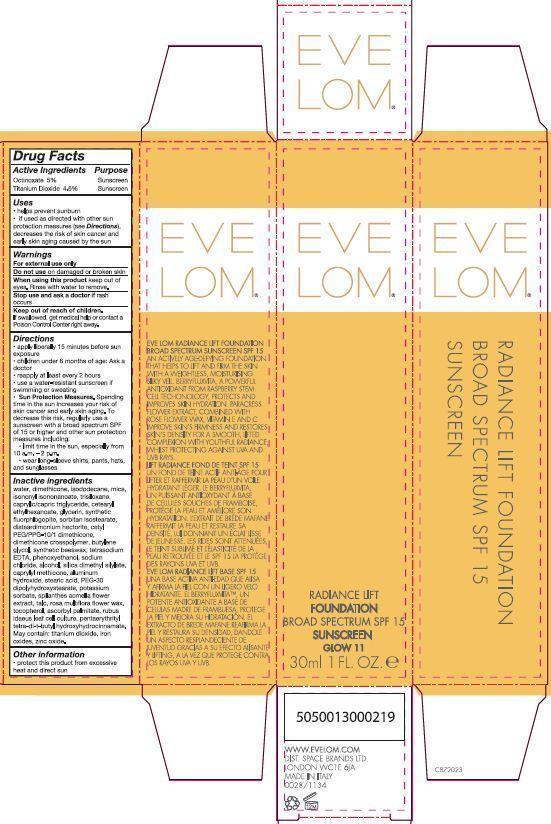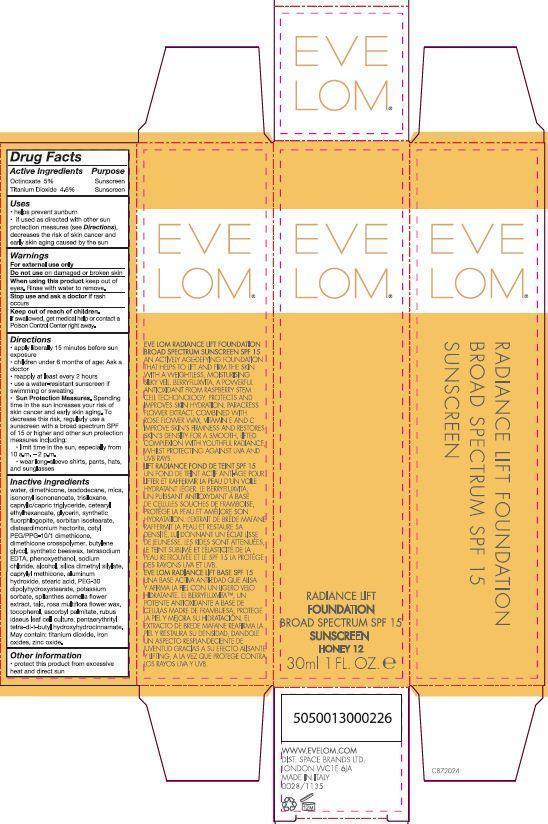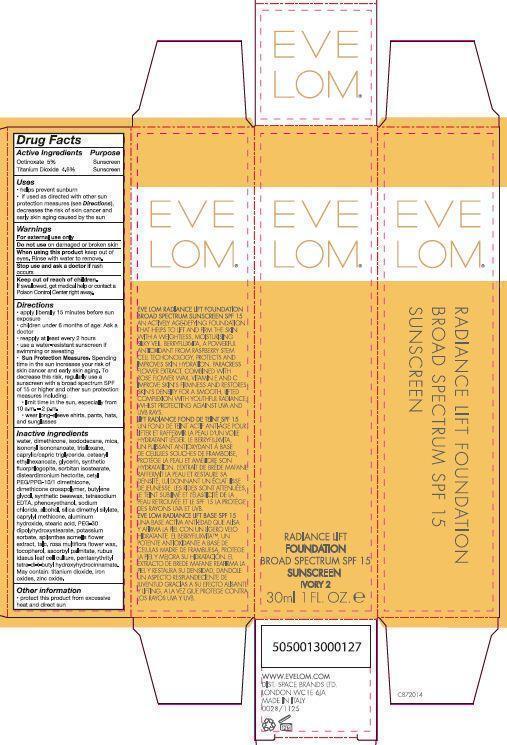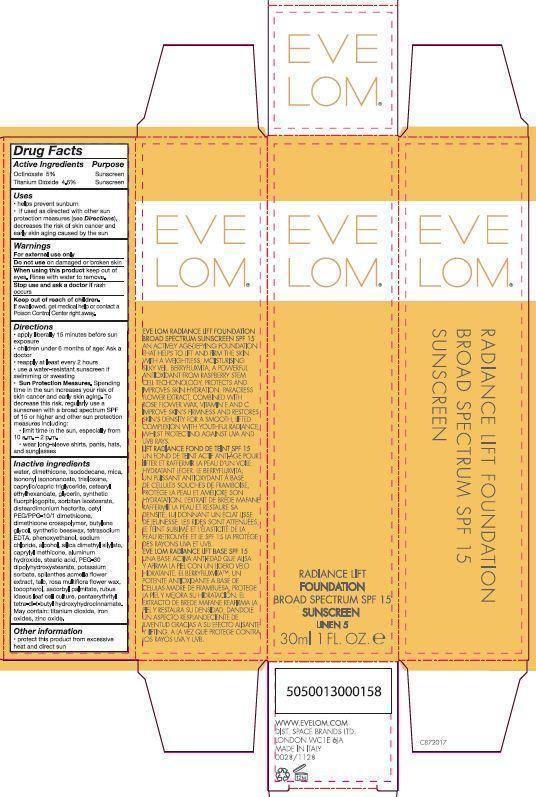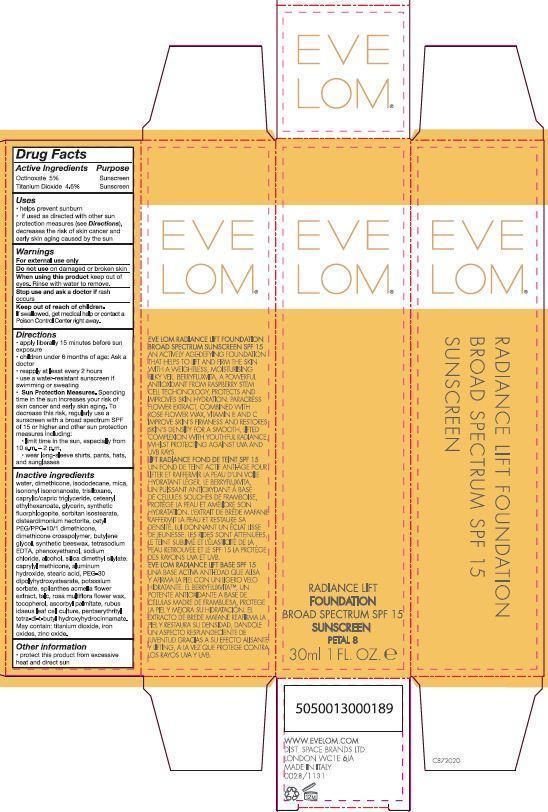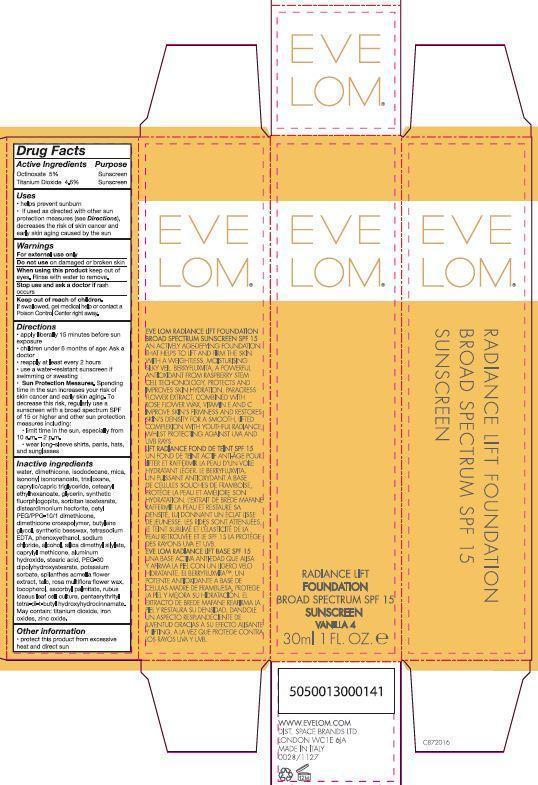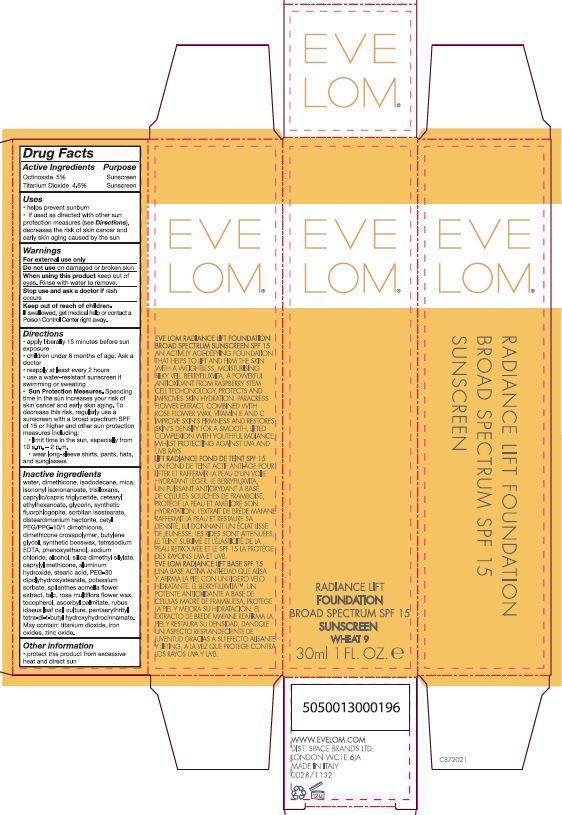 DRUG LABEL: Eve Lom Radiance Lift Foundation SPF 15
NDC: 61601-1125 | Form: CREAM
Manufacturer: Space Brands Limited
Category: otc | Type: HUMAN OTC DRUG LABEL
Date: 20140319

ACTIVE INGREDIENTS: TITANIUM DIOXIDE 1.38 g/30 mL; OCTINOXATE 1.5 g/30 mL
INACTIVE INGREDIENTS: WATER; DIMETHICONE; ISODODECANE; MICA; ISONONYL ISONONANOATE; TRISILOXANE; FERRIC OXIDE YELLOW; MEDIUM-CHAIN TRIGLYCERIDES; CETEARYL ETHYLHEXANOATE; GLYCERIN; SORBITAN ISOSTEARATE; DISTEARDIMONIUM HECTORITE; CETYL PEG/PPG-10/1 DIMETHICONE (HLB 3); BUTYLENE GLYCOL; EDETATE SODIUM; FERRIC OXIDE RED; PHENOXYETHANOL; SODIUM CHLORIDE; ALCOHOL; ZINC OXIDE; SILICA DIMETHYL SILYLATE; ALUMINUM HYDROXIDE; STEARIC ACID; CAPRYLYL TRISILOXANE; PEG-30 DIPOLYHYDROXYSTEARATE; FERROSOFERRIC OXIDE; POTASSIUM SORBATE; TALC; ACMELLA OLERACEA FLOWER; ROSA MULTIFLORA FLOWER WAX; TOCOPHEROL; ASCORBYL PALMITATE; PENTAERYTHRITOL TETRAKIS(3-(3,5-DI-TERT-BUTYL-4-HYDROXYPHENYL)PROPIONATE)

Eve Lom® Radiance Lift Foundation SPF 15

Drug Facts

Active Ingredients Purpose

Octinoxate 5% Sunscreen

Titanium Dioxide 4.6% Sunscreen

Uses

- helps prevent sunburn
- if used as directed with other sun protection measure (see Directions), decreases the risk of skin cancer and early skin aging caused by the sun

Warnings

For external use only

Do not use on damaged or broken skin

When using this product keep out of eyes. Rinse with water to remove.

Stop use and ask a doctor if rash occurs.

Keep out of reach of children. If swallowed, get medical help or contact a Poison Control Center right away.

Directions

- apply liberally 15 minutes before sun exposure
- children under 6 months of age: Ask a doctor
- reapply at least every 2 hours
- use a water-resistant sunscreen if swimming or sweating
- Sun Protection Measures. Spending time in the sun increases your risk of skin cancer and early skin aging. To decrease this risk, regularly use a sunscreen with a broad spectrum SPF of 15 or higher and other sun protection measures including:
  - limit time in the sun, especially from 10 a.m. – 2 p.m.
  - wear long-sleeve shirts, pants, hats, and sunglasses

INACTIVE INGREDIENT

water, dimethicone, isododecane, mica, isononyl isononanoate, trisiloxane, caprylic/capric triglyceride, cetearyl ethlyhexanoate, glycerin, synthetic fluorphlogopite, sorbitan isostearate, disteardimonium hectorite, cetyl PEG/PPG-10/1 dimethicone, dimethicone crosspolymer, butylene glycol, synthetic beeswax, tetrasodium EDTA, phenoxyethanol, sodium chloride, alcohol, silica dimethyl silylate, caprylyl methicone, aluminum hydroxide, stearic acid, PEG-30 dipolyhydroxystearate, potassium sorbate, spilanthes acmella flower extract, talc, rosa multiflora flower wax, tocopherol, ascorbyl palmitate, rubus idaeus leaf cell culture, pentaerythrityl tetra-di-t-butyl hydroxyhydrocinnamate.

May contain: titanium dioxide, iron oxides, zinc oxide.

STORAGE AND HANDLING

- protect this product from excessive heat and direct sun

PRINCIPAL DISPLAY PANEL - 30 mL Bottle Carton - Ivory

EVE LOM®

RADIANCE LIFT

FOUNDATION

BROAD SPECTRUM SPF 15

SUNSCREEN

IVORY 2

30 ml 1 FL. OZ. e

PRINCIPAL DISPLAY PANEL - 30 mL Bottle Carton - Ecru

EVE LOM®

RADIANCE LIFT

FOUNDATION

BROAD SPECTRUM SPF 15

SUNSCREEN

ECRU 3

30 ml 1 FL. OZ. e

PRINCIPAL DISPLAY PANEL - 30 mL Bottle Carton - Vanilla

EVE LOM®

RADIANCE LIFT

FOUNDATION

BROAD SPECTRUM SPF 15

SUNSCREEN

VANILLA 4

30 ml 1 FL. OZ. e

PRINCIPAL DISPLAY PANEL - 30 mL Bottle Carton - Linen

EVE LOM®

RADIANCE LIFT

FOUNDATION

BROAD SPECTRUM SPF 15

SUNSCREEN

LINEN 5

30 ml 1 FL. OZ. e

PRINCIPAL DISPLAY PANEL - 30 mL Bottle Carton - Cream

EVE LOM®

RADIANCE LIFT

FOUNDATION

BROAD SPECTRUM SPF 15

SUNSCREEN

CREAM 6

30 ml 1 FL. OZ. e

PRINCIPAL DISPLAY PANEL - 30 mL Bottle Carton - Beige

EVE LOM®

RADIANCE LIFT

FOUNDATION

BROAD SPECTRUM SPF 15

SUNSCREEN

BEIGE 7

30 ml 1 FL. OZ. e

PRINCIPAL DISPLAY PANEL - 30 mL Bottle Carton - Petal

EVE LOM®

RADIANCE LIFT

FOUNDATION

BROAD SPECTRUM SPF 15

SUNSCREEN

PETAL 8

30 ml 1 FL. OZ. e

PRINCIPAL DISPLAY PANEL - 30 mL Bottle Carton - Wheat

EVE LOM®

RADIANCE LIFT

FOUNDATION

BROAD SPECTRUM SPF 15

SUNSCREEN

WHEAT 9

30 ml 1 FL. OZ. e

PRINCIPAL DISPLAY PANEL - 30 mL Bottle Carton - Bamboo

EVE LOM®

RADIANCE LIFT

FOUNDATION

BROAD SPECTRUM SPF 15

SUNSCREEN

BAMBOO 10

30 ml 1 FL. OZ. e

PRINCIPAL DISPLAY PANEL - 30 mL Bottle Carton - Glow

EVE LOM®

RADIANCE LIFT

FOUNDATION

BROAD SPECTRUM SPF 15

SUNSCREEN

GLOW 11

30 ml 1 FL. OZ. e

PRINCIPAL DISPLAY PANEL - 30 mL Bottle Carton - Honey

EVE LOM®

RADIANCE LIFT

FOUNDATION

BROAD SPECTRUM SPF 15

SUNSCREEN

HONEY 12

30 ml 1 FL. OZ. e

PRINCIPAL DISPLAY PANEL - 30 mL Bottle Carton - Alabaster

EVE LOM®

RADIANCE LIFT

FOUNDATION

BROAD SPECTRUM SPF 15

SUNSCREEN

ALABASTER 1

30 ml 1 FL. OZ. e